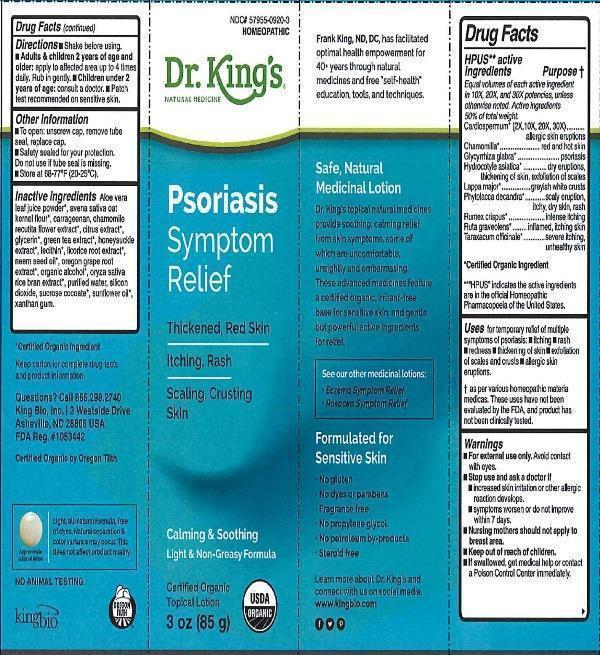 DRUG LABEL: Psoriasis Symptom Relief
NDC: 57955-0920 | Form: CREAM
Manufacturer: King Bio Inc.
Category: homeopathic | Type: HUMAN OTC DRUG LABEL
Date: 20170120

ACTIVE INGREDIENTS: CARDIOSPERMUM HALICACABUM FLOWERING TOP 2 [hp_X]/85 g; MATRICARIA RECUTITA 10 [hp_X]/85 g; GLYCYRRHIZA GLABRA 10 [hp_X]/85 g; CENTELLA ASIATICA 10 [hp_X]/85 g; ARCTIUM LAPPA ROOT 10 [hp_X]/85 g; PHYTOLACCA AMERICANA ROOT 10 [hp_X]/85 g; RUMEX CRISPUS ROOT 10 [hp_X]/85 g; RUTA GRAVEOLENS FLOWERING TOP 10 [hp_X]/85 g; TARAXACUM OFFICINALE 10 [hp_X]/85 g
INACTIVE INGREDIENTS: ALOE VERA LEAF; OATMEAL; CHONDRUS CRISPUS CARRAGEENAN; CHAMOMILE; CITRUS BIOFLAVONOIDS; GLYCERIN; GREEN TEA LEAF; LONICERA JAPONICA FLOWER; LECITHIN, SOYBEAN; LICORICE; AZADIRACHTA INDICA SEED OIL; MAHONIA AQUIFOLIUM ROOT; ALCOHOL; RICE BRAN; WATER; SILICON DIOXIDE; SUCROSE COCOATE; SUNFLOWER OIL; XANTHAN GUM

Psoriasis Symptom Relief

ACTIVE INGREDIENT

Drug Facts__________________________________________________________________________________________________________

HPUS active ingredient Purpose†

Equal volumes of each active ingredient in 10X, 20X, and 30X potencies, unless otherwise noted.

Active ingredients 50% of total weight.

Cardiospermum* (2X, 10X, 20X, 30X), Chamomilla*, Glycyrrhiza glabra, Hydrocotyle asiatica*, Lappa major*, Phytolacca decandra*, Rumex crispus*, Ruta graveolens*, Taraxacum officinale*.

*Certified Organic ingredient

*"HPUS" indicates the active ingredients are in the official Homeopathic Pharmacopoeia of the United States.

INDICATIONS AND USAGE

Uses for temporary relief of multiple symptoms of psoriasis: •itching •rash •redness •thickening of skin •exfoliation of scales and crusts •allergic skin eruptions.

† as per various homeopathic materia medicas. These uses have not been evaluated by the FDA, and product has not been clinically tested.

Warnings

- For external use only. Avoid contact with eyes.
- Stop use and ask a doctor if •increased skin irritation or other allergic reaction develops. •symptoms worsen or do not improve within 7 days.
- Nursing mothers should not apply to breast area.
- Keep out of reach of children.
- If swallowed, get medical help or contact a Poison Control Center immediately.

- Keep out of reach of children.

Directions

•Shake before using. •Adults & children 2 years of age and older: apply to affected area up to 4 times daily. Rub in gently. •Children under 2 years of age: consult a doctor. •Patch test recommended on sensitive skin.

Other information:

- To open: unscrew cap, remove tube seal, replace cap.
- Safety sealed for your protection.
- Do not use if tube seal is missing.
- Store at 68-77° (20-25°C).
- Certified organic topical lotion.

INACTIVE INGREDIENT

Inactive ingredients: Aloe vera leaf juice powder*, avena sativa oat kernel flour*, carrageenan, chamomile recutita flower extract*, citrus extract*, glycerin, green tea extract*, honeysuckle extract*, lecithin*, licorice root extract*, neem seed oil*, oregon grape root extract*, organic alcohol*, oryza sativa race bran extract*, silicon dioxide, sucrose cocoate, sunflower oil*, water, xanthan gum.

*Certified organic Ingredient.

Certified organic by Oregon Tilth.

PURPOSE

__________________________________________________________________________________________________________

HPUS active ingredient Purpose†

Equal volumes of each active ingredient in 10X, 20X, and 30X potencies, unless otherwise noted.

Active ingredients 50% of total weight.

Cardiospermum* (2X, 10X, 20X, 30X).....................................................allergic skin eruptions

Chamomilla.................................................................................................red and hot skin

Glycyrrhiza glabra*.................................................................................................psoriasis

Hydrocotyle asiatica*.................................dry eruptions, thickening of skin, exfoliation of scales

Lappa major...........................................................................................greyish white crusts

Phytolacca decandra...........................................................scaly eruption, itchy, dry skin, rash

Rumex crispus................................................................................................intense itching

Ruta graveolens....................................................................................inflamed, itching skin

Taraxacum officinale...................................................................severe itching, unhealthy skin